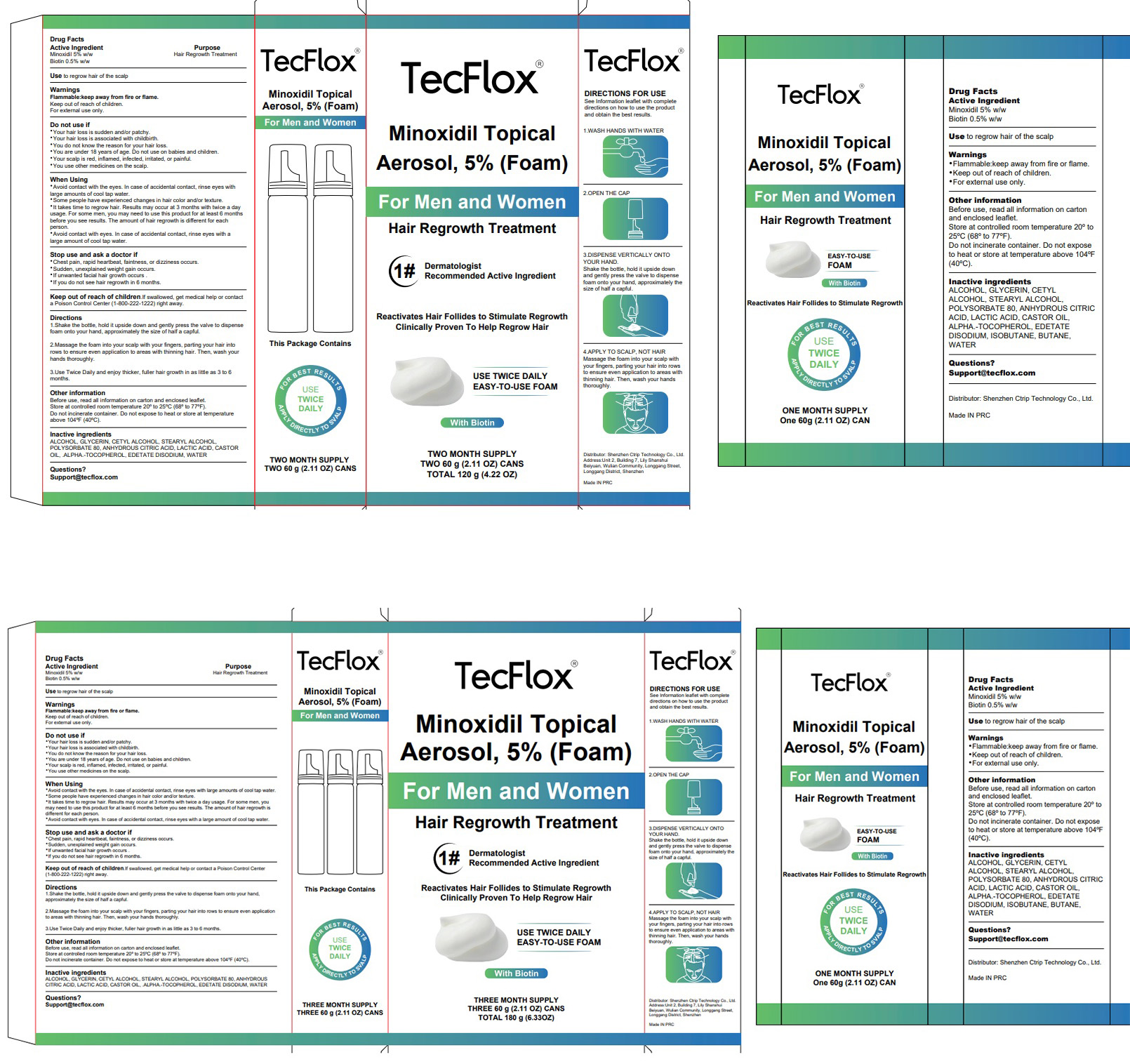 DRUG LABEL: 5% Minoxidil Hair Growth Foam with Biotin
NDC: 84614-003 | Form: AEROSOL, FOAM
Manufacturer: Shenzhen Ctrip Technology Co., Ltd.
Category: otc | Type: HUMAN OTC DRUG LABEL
Date: 20250912

ACTIVE INGREDIENTS: BIOTIN 0.5 g/100 g; MINOXIDIL 5 g/100 g
INACTIVE INGREDIENTS: BUTANE; ALCOHOL; WATER; ANHYDROUS CITRIC ACID; LACTIC ACID; CETYL ALCOHOL; GLYCERIN; STEARYL ALCOHOL; POLYSORBATE 80; .ALPHA.-TOCOPHEROL; ISOBUTANE; CASTOR OIL; EDETATE DISODIUM

84614-003 5% Minoxidil Hair Growth Foam with Biotin

5% Minoxidil Hair Growth Foam with Biotin

ACTIVE INGREDIENT

Minoxidil 5%
Biotin 0.5%

PURPOSE

Hair Regrowih Treaiment

INDICATIONS AND USAGE

Use to regrow hair of the scalp

WARNINGS

Flammable:keep away from fire or flame.
Keep out of reach of children.
For exlernal use oniy

DO NOT USE

Your hair loss is gudden andlor palchy.
Your hair loss is associald with chidbinth.
You do nol knaw the reason for your hair logs.
You are under 18 years of age. Do not use on babies and children.
Your gcalp is red, intamed, infecled, irritated, or painfu.
You use other medicines on the scalp.

WHEN USING

Awoid contact with the eyes. in case of accidenlal conlact, rinse eyes withlarge amcunts of cool tap waler.
Some people have experienced changes in hair color andlor lexture.
It takes time lo regrow hair, Resuts may ooour at 3 monihs with twice a dayusage. For some men, you may need to use this product for at least 6 monlhsbefore you see results. The amount of hair regrowih is diferent for eachpergon.
Awoid contact with eyes. in case of aocidenlal contact, rinse eyes with alarge amcunt of cool tap waler.

STOP USE

Chest pain, rapid hearibeat, aininegs, or dizziness oocurs.
Sudden, unexplained weight gain oocurs.
If umwaneed facil har growth occurs .
lf you do nat see hair regrowth in 6 months.

Keep out of reach of children.lf swalkwed, get medical help or contac a Poison Conlrol Cenler(1-800-222-1222) right away.

DOSAGE AND ADMINISTRATION

1.Shake the bollle, hold it upside down and genlly press the walve to dispensefoam onio your hand, approximalely the size of half a capful
2.Massage the foam inio your gcalp with your fngers, paring your hair intorows to ensure even application to areas with thinning hair. Then, wash yourhands thoroughly.
3.Use Twice Daily and enjoy thicker, fuler hair gronth in as lille as 3 to 6months.

STORAGE AND HANDLING

Before use, read al informglion on carton and enclosed leale.Store at conlrolled room temperalure 20° lo 25°℃ (68° to 77°F)Do not incinerale container. Do not expose to heat or slore at lemperalureabove 104° F(40°C).

INACTIVE INGREDIENT

ALCOHOL
GLYCERIN
CETYL ALCOHOL
STEARYL ALCOHOL
POLYSORBATE 80
ANHYDROUS CITRIC ACID
LACTIC ACID
CASTOR OIL
.ALPHA.-TOCOPHEROL
EDETATE DISODIUM
ISOBUTANE
BUTANE
WATER